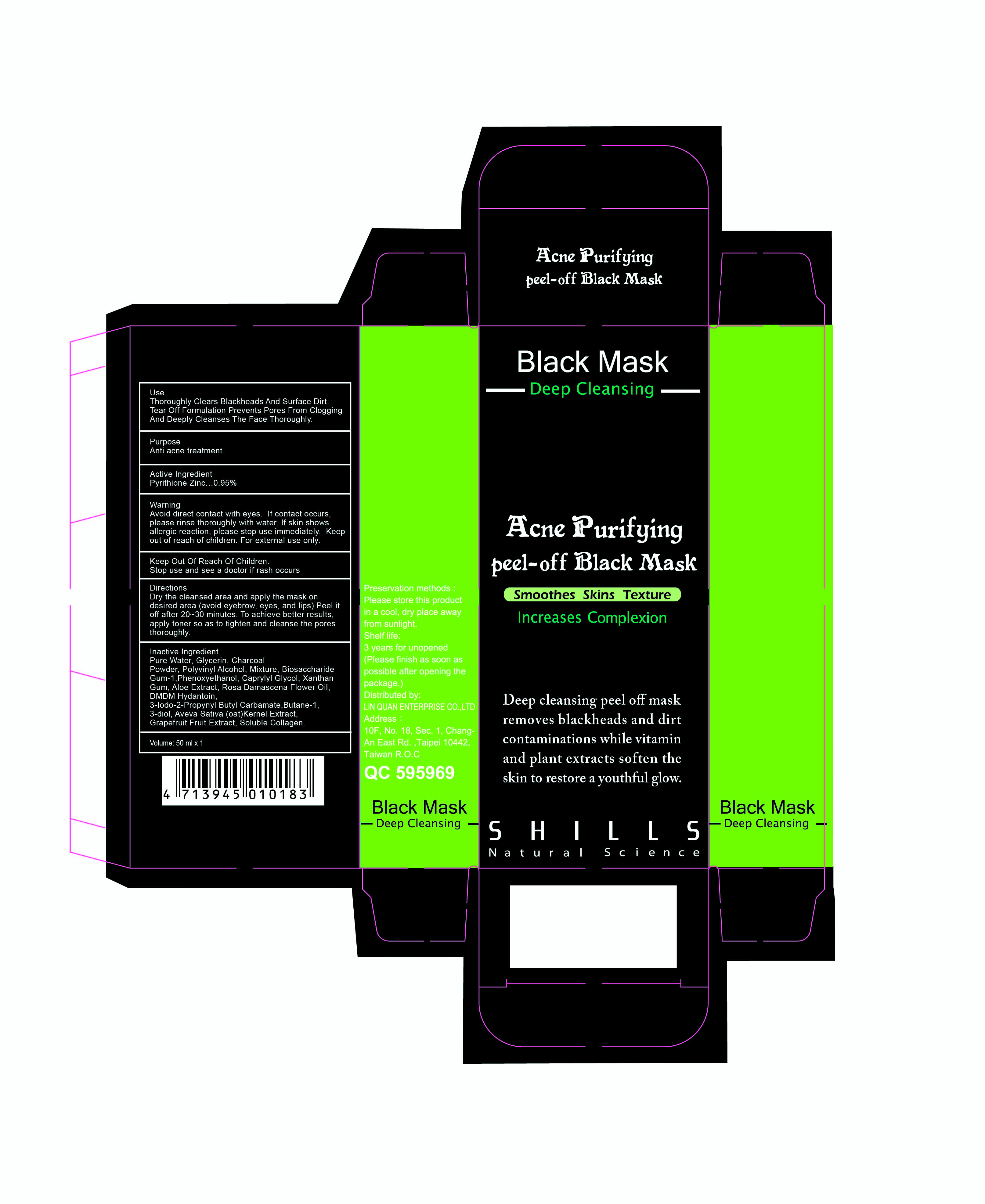 DRUG LABEL: SHILLS ACNE Purifying Peel Off Black Mask
NDC: 71696-001 | Form: SOLUTION
Manufacturer: Lin Quan Enterprises Co., Ltd.
Category: otc | Type: HUMAN OTC DRUG LABEL
Date: 20180428

ACTIVE INGREDIENTS: PYRITHIONE ZINC 0.95 g/100 mL
INACTIVE INGREDIENTS: GLYCERIN; WATER; ACTIVATED CHARCOAL; POLYVINYL ALCOHOL, UNSPECIFIED; BIOSACCHARIDE GUM-1; PHENOXYETHANOL; CAPRYLYL GLYCOL; XANTHAN GUM; ALOE; ROSA DAMASCENA FLOWER OIL; DMDM HYDANTOIN; OAT KERNEL OIL; GRAPEFRUIT; MARINE COLLAGEN, SOLUBLE

Drug Fact

Active Ingredient:

Pyrithione Zinc 0.95%

Purpose:

Acne Treatment

Uses:

Thoroughly clears blackheads and surface dirts. Tear off formulation prevents pores from clogging and deeplycleanes the face thoroughly

Warning:

Aviod direct contact with eyes. If contacts occurs, please rinse thoroughly with water. If skin shows allergic reaction, please st5op use immediately. For external use only.

Stop use and ask a doctor If

rash occurs

Keep Out of Reach of Children

Directions:

Dry the cleansed area and apply the mask on direct area (avoid eyebrow, eyes, and lips). Peel it off and 20-30 minutes. To achieve better results, apply toner so as to tighten and cleanse the pores thoroughly.

Inactive Ingredient:

Purified Water, Glycerin, Charcoal Powder, Polyvinyl Alcohol, Biosaccharide Gum-1, Phenoxyethanol, Caprylyl Glycol, Xanthan Gum, Aloe Extract, Rosa Damascena Flower Oil, DMDM Hydantoin, 3-Iodo-2-Propynyl Butyl Carbamate, Butane-1,3-diol, Aveva Sativa (Oat) Kernel Extract, Grapefruit Extract, Soluble Collagen